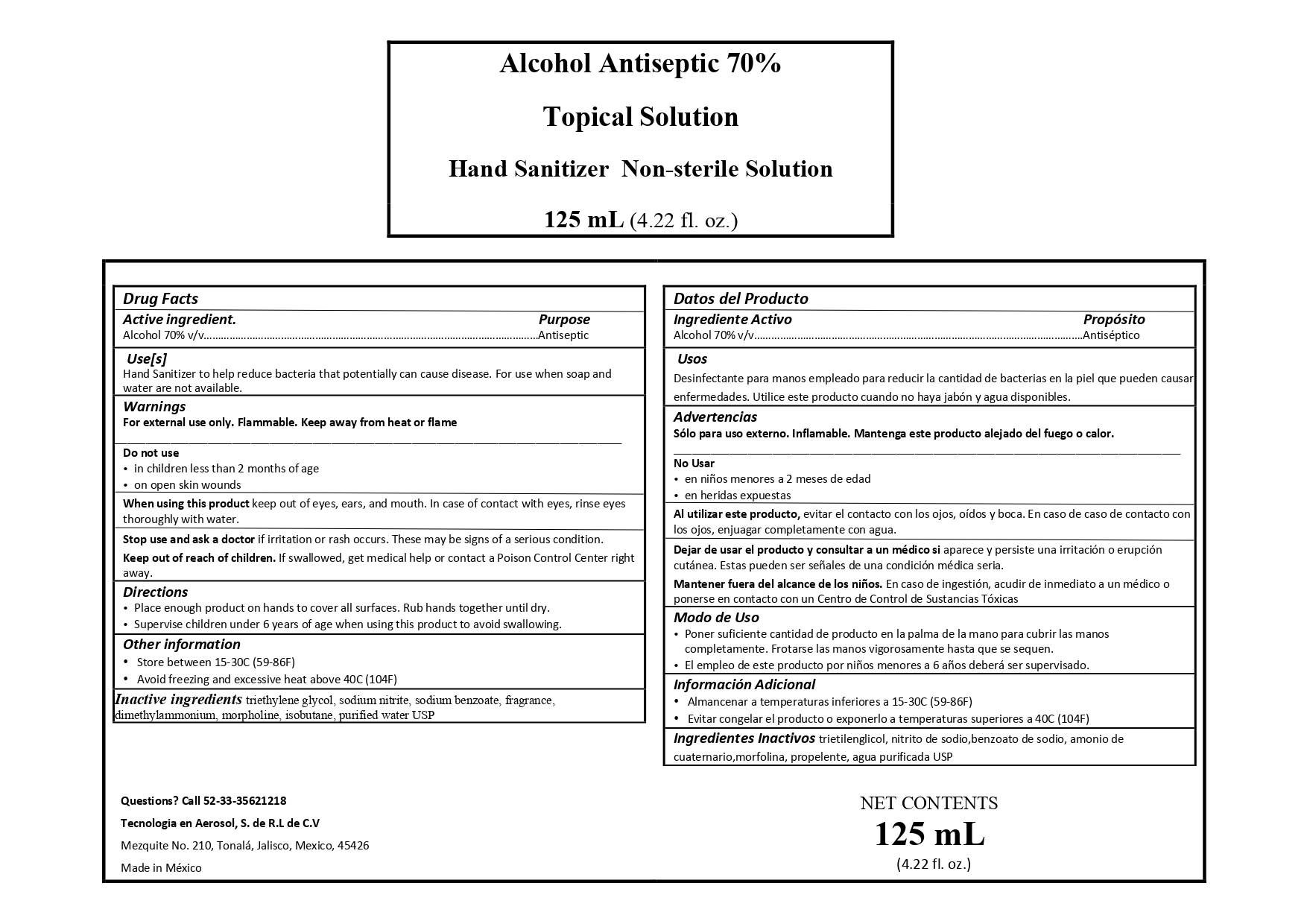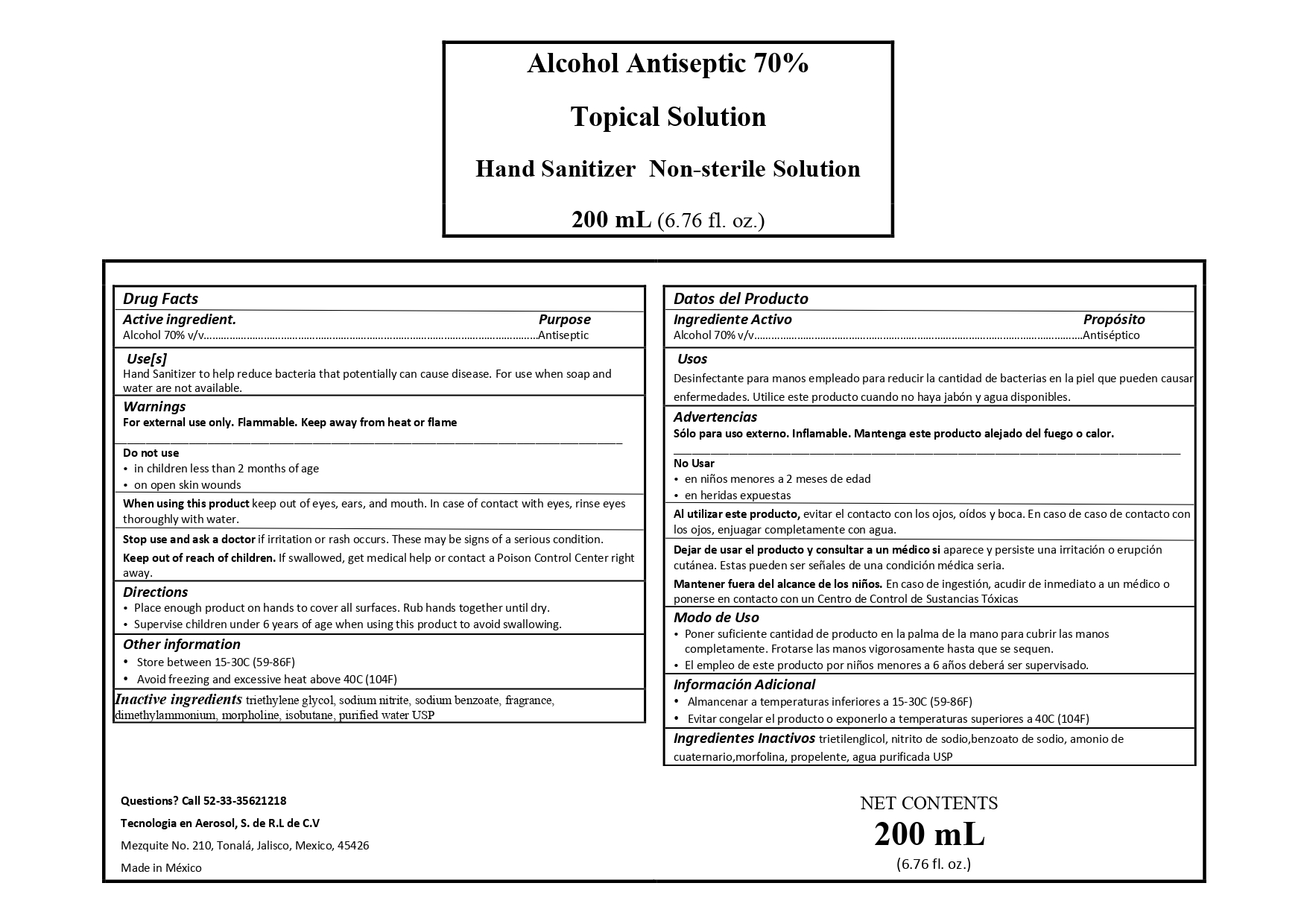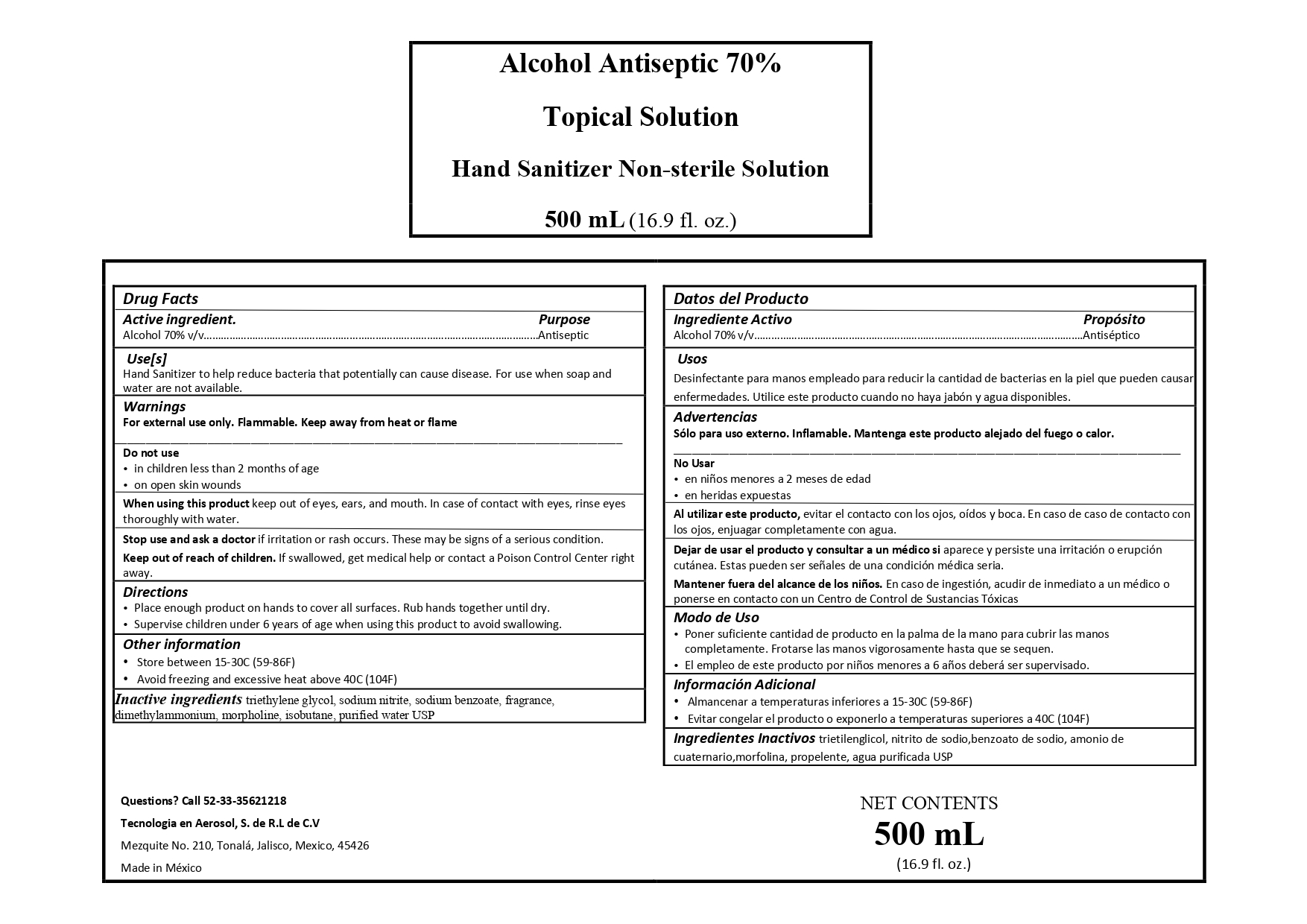 DRUG LABEL: Hand Sanitizer
NDC: 78358-001 | Form: AEROSOL, SPRAY
Manufacturer: Tecnología en Aerosol, S. de R.L. de C.V.
Category: otc | Type: HUMAN OTC DRUG LABEL
Date: 20200522

ACTIVE INGREDIENTS: ALCOHOL 70 mL/100 mL
INACTIVE INGREDIENTS: TRIETHYLENE GLYCOL 6 mL/100 mL; SODIUM NITRITE 0.09 mL/100 mL; WATER; SODIUM BENZOATE 0.09 mL/100 mL; 2,4,5-T DIMETHYLAMMONIUM 0.4 mL/100 mL; 2,4-D MORPHOLINE 0.1 mL/100 mL; ISOBUTANE 28 mL/100 mL

Hand Sanitizer

The hand sanitizer is manufactured using only the following United States Pharmacopoeia (USP) grade ingredients in the preparation of the product (percentage in final product formulation) consistent with World Health Organization (WHO) recommendations:

Alcohol (ethanol) (USP or Food Chemical Codex (FCC) grade) (70%, volume/volume (v/v)) in an aqueous solution denatured according to Alcohol and Tobacco Tax and Trade Bureau regulations in 27 CFR part 20.

Sodium nitrite (0.09% v/v).

Sodium Benzoate (0.9% v/v).

Dimethylammonium (0.4% v/v)

Morpholine (o.1% v/v)

Triethylene Glycol (6.9% v/v)

Isobutane (28.00% v/v)

Sterile distilled water or boiled cold water.

The firm does not add other active or inactive ingredients. Different or additional ingredients may impact the quality and potency of the product.

Active Ingredient(s)

Alcohol 70% v/v. Purpose: Antiseptic

Purpose

Antiseptic, Hand Sanitizer

Use

Hand Sanitizer to help reduce bacteria that potentially can cause disease. For use when soap and water are not available.

Warnings

For external use only. Flammable. Keep away from heat or flame

Do not use

- in children less than 2 months of age
- on open skin wounds

When using this product keep out of eyes, ears, and mouth. In case of contact with eyes, rinse eyes thoroughly with water.
Stop use and ask a doctor if irritation or rash occurs. These may be signs of a serious condition.
Keep out of reach of children. If swallowed, get medical help or contact a Poison Control Center right away.

Stop use and ask a doctor if irritation or rash occurs. These may be signs of a serious condition.

Keep out of reach of children. If swallowed, get medical help or contact a Poison Control Center right away.

Directions

- Place enough product on hands to cover all surfaces. Rub hands together until dry.
- Supervise children under 6 years of age when using this product to avoid swallowing.

Other information

- Store between 15-30C (59-86F)
- Avoid freezing and excessive heat above 40C (104F)

Inactive ingredients

sodium nitrate, sodium benzoate, dimethylammonium, morpholine, triethylene glycol, isobutane, purified water USP

Package Label - Principal Display Panel

200 mL NDC: 78358-001-02

PACKAGE LABEL

500 ml NDC 78358-001-03